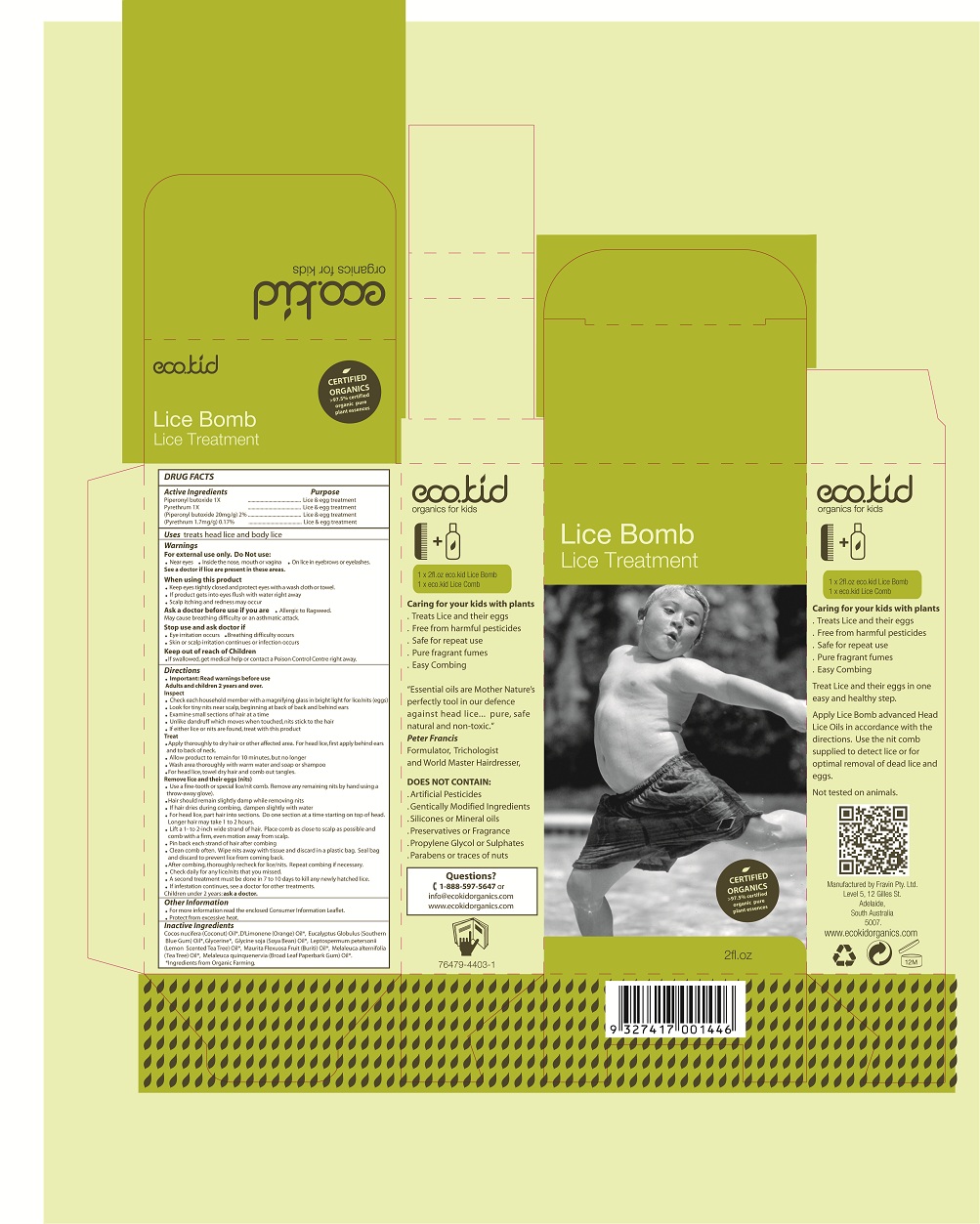 DRUG LABEL: Eco.kid
NDC: 76479-4403 | Form: SHAMPOO
Manufacturer: Fravin Pty Ltd
Category: otc | Type: HUMAN OTC DRUG LABEL
Date: 20111128

ACTIVE INGREDIENTS: PIPERONYL BUTOXIDE 2 mL/100 mL; PYRETHRUM EXTRACT 0.17 mL/100 mL
INACTIVE INGREDIENTS: COCONUT OIL; ORANGE OIL; EUCALYPTUS OIL; GLYCERIN; SOYBEAN OIL; LEPTOSPERMUM PETERSONII LEAF OIL; MAURITIA FLEXUOSA FRUIT OIL; TEA TREE OIL; MELALEUCA QUINQUENERVIA LEAF OIL

Active Ingredients Purpose

Piperonyl butoxide 1X Lice and egg treatment

Pyrethrum 1X Lice and egg treatment

(Piperonyl butoxide 20mg/g) 2% Lice and egg treatment

(Pyrethrum 1.7mg/g) 0.17% Lice and egg treatment

PURPOSE

Lice Treatment

Warnings

For external use only.

Do Not Use:

- Near eyes
- Inside the nose, mouth, or vagina
- On lice in eyebrows or eyelashes.

See a doctor if lice are present in these areas.

When using this product

- Keep eyes tightly closed and protect eyes with a wash cloth or towel.
- If product gets into eyes flush with water right away
- Scalp itching and redness may occur

Ask a doctor before use if you are

- Allergic to ragweed. May cause breathing difficulty or an asthmatic attack.

Stop use and ask doctor if

- Eye irritation occurs
- Breathing difficulty occurs
- Skin or scalp irritation continues or infection occurs

Keep out of reach of Children

- If swallowed, get medical help or contact a Poison Control Centre right away.

INDICATIONS AND USAGE

Uses treats head lice and body lice

Other Information

- For more information read the enclosed Consumer Information Leaflet.
- Protect from excessive heat.

Inactive Ingredients

Cocos nucifera (Coconut) Oil*, D'Limonene (Orange) Oil*, Eucalyptus Globulus (Southern
Blue Gum) Oil*, Glycerine*, Glycine soja (Soya Bean) Oil*, Leptospermum petersonii
(Lemon Scented Tea Tree) Oil*, Maurita Flexuosa Fruit (Buriti) Oil*, Melaleuca alternifolia
(Tea Tree) Oil*, Melaleuca quinquenervia (Broad Leaf Paperbark Gum) Oil*.
*Ingredients from Organic Farming.

Directions

- Important: Read warnings before use

Adults and children 2 years and over.
Inspect

- Check each household member with a magnifying glass in bright light for lice/nits (eggs)
- Look for tiny nits near scalp, beginning at back of back and behind ears
- Examine small sections of hair at a time
- Unlike dandruff which moves when touched, nits stick to the hair
- If either lice or nits are found, treat with this product

Treat

- Apply thoroughly to dry hair or other affected area. For head lice, first apply behind ears
  and to back of neck.
- Allow product to remain for 10 minutes, but no longer
- Wash area thoroughly with warm water and soap or shampoo
- For head lice, towel dry hair and comb out tangles.

Remove lice and their eggs (nits)

- Use a fine-tooth or special lice/nit comb. Remove any remaining nits by hand using a
  throw-away glove).
- Hair should remain slightly damp while removing nits
- If hair dries during combing, dampen slightly with water
- For head lice, part hair into sections. Do one section at a time starting on top of head.
  Longer hair may take 1 to 2 hours.
- Lift a 1- to 2-inch wide strand of hair. Place comb as close to scalp as possible and
  comb with a firm, even motion away from scalp.
- Pin back each strand of hair after combing
- Clean comb often. Wipe nits away with tissue and discard in a plastic bag. Seal bag
  and discard to prevent lice from coming back.
- After combing, thoroughly recheck for lice/nits. Repeat combing if necessary.
- Check daily for any lice/nits that you missed.
- A second treatment must be done in 7 to 10 days to kill any newly hatched lice.
- If infestation continues, see a doctor for other treatments.

Children under 2 years: ask a doctor.